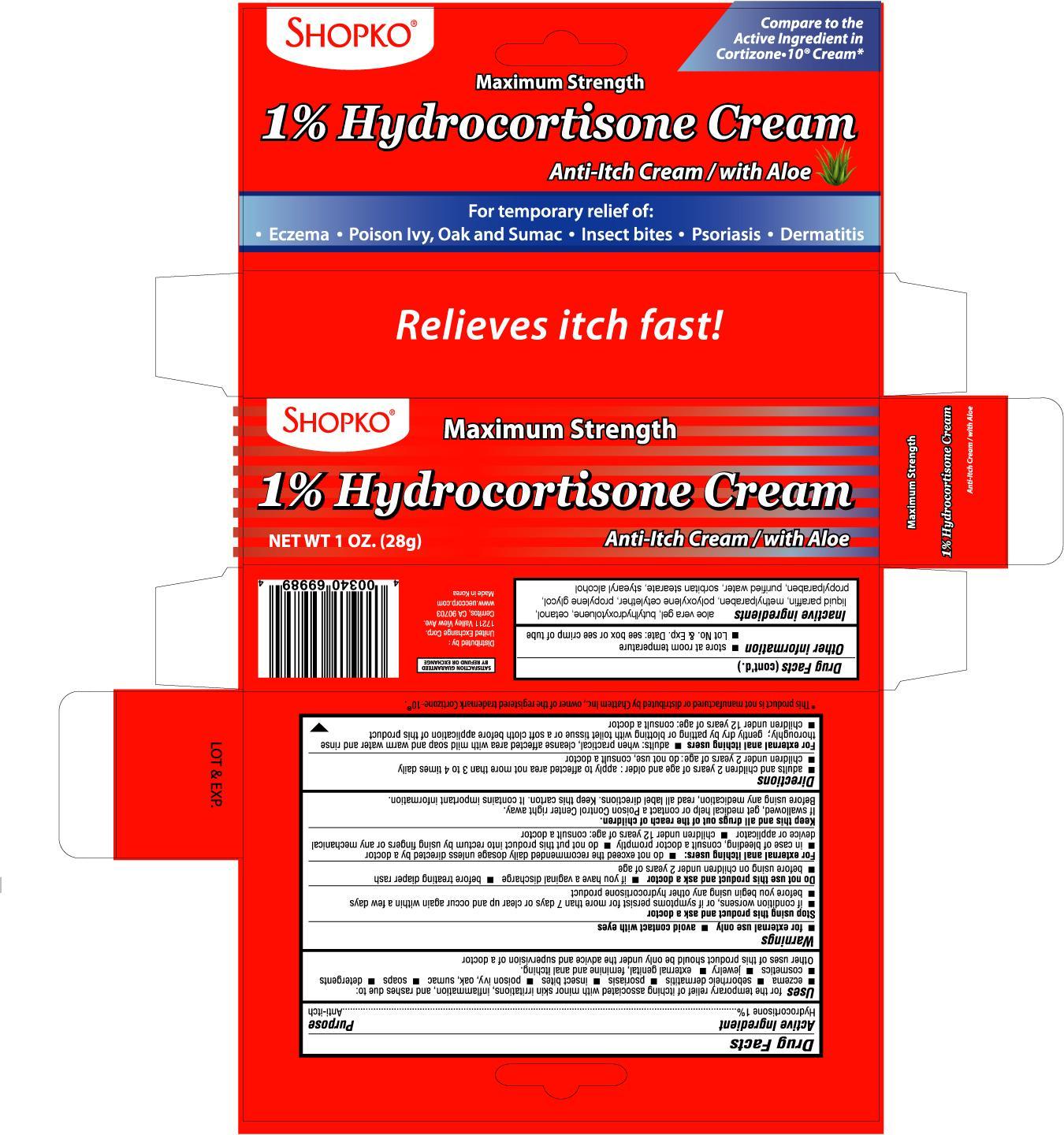 DRUG LABEL: SHOPKO HYDROCORTISONE WITH ALOE
NDC: 65923-699 | Form: CREAM
Manufacturer: UNITED EXCHANGE CORP
Category: otc | Type: HUMAN OTC DRUG LABEL
Date: 20121231

ACTIVE INGREDIENTS: HYDROCORTISONE 1 g/100 g
INACTIVE INGREDIENTS: ALOE VERA LEAF; BUTYLATED HYDROXYTOLUENE; MINERAL OIL; METHYLPARABEN; PROPYLENE GLYCOL; PROPYLPARABEN; WATER; STEARYL ALCOHOL

Drug Facts

Active ingredient Purpose

Hydrocortisone 1%....................................................................Anti-itch

PURPOSE

Uses for the temporary relief of itching associated with minor skin irritations, inflammation and rashes due to:

- eczema
- seborrheic dermatitis
- psoriasis
- insect bites
- poison ivy, oak, sumac
- soaps
- detergents
- cosmetics
- jewelry
- external genital, feminine and anal itching.

Other uses of this product should be only under the advice and supervision of a doctor

Warnings

- for external use only
- avoid contact with eyes

Stop using this product and ask a doctor

- if condition worsens, or if symptoms persist for more than 7 days or clear up and occur again within a few days
- before you begin using any other hydrocortisone product

Do not use this product and ask a doctor

- if you have a vaginal discharge
- before treating diaper rash
- before using on children under 2 years of age

KEEP OUT OF REACH OF CHILDREN

Keep this and all drugs out of the reach of children.

If swallowed, get medical help or contact a Poison Control Center right away.

Before using any medication, read all label directions. Keep this carton. It contains important information.

Directions

- for adults and children 2 years of age and older: apply to affected area not more than 3 to 4 times daily
- children under 2 years of age: do not use, consult a doctor

Other information

- store at room temperature
- Lot No. and Exp. Date: see box or see crimp of tube

Inactive ingredients

Aloe Vera Gel, Butylated Hydroxytoluene, Cetanol, Liquid Paraffin, Methylparaben, Polyonyethylene Cetylether, Propylene Glycol, Propylparaben, Purified Water, Sorbitan Monostearate, Stearyl Alcohol

DOSAGE AND ADMINISTRATION

Distributed by:

United Exchange Corp

17211 Valley View Ave.

Cerritos, CA 90703

www.ueccorp.com

Made in Korea